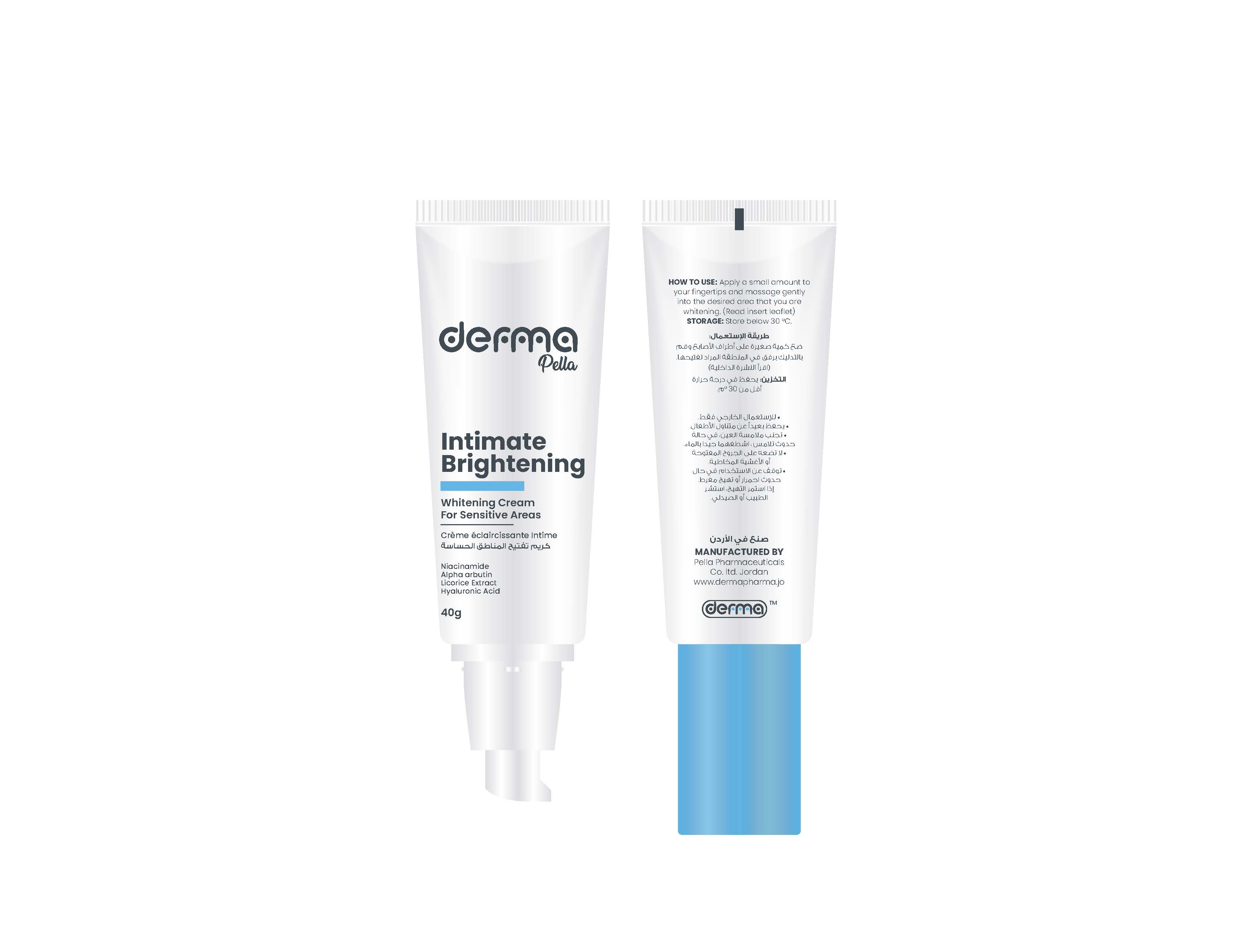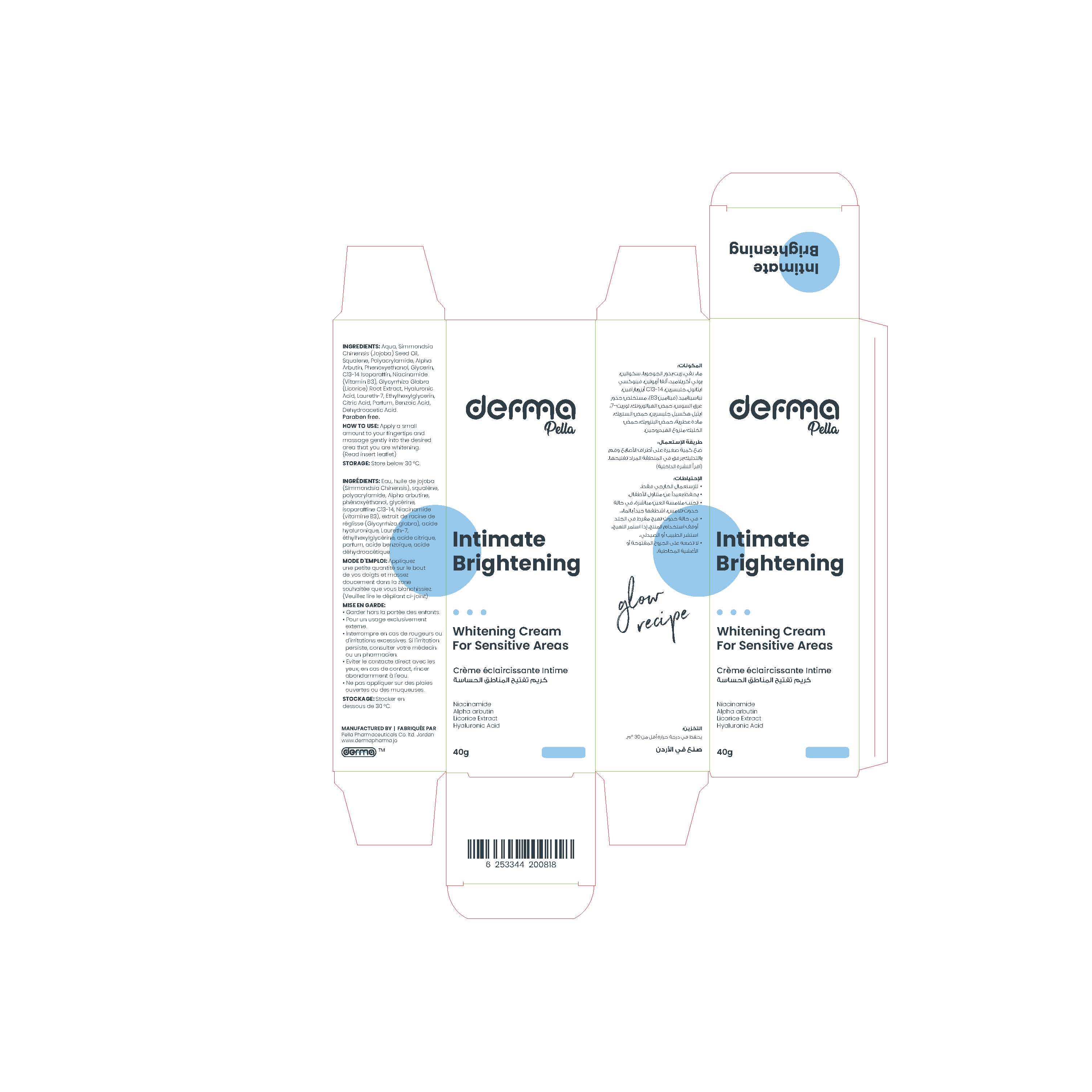 DRUG LABEL: Derma Pella Intimate Brightening
NDC: 82160-818 | Form: CREAM
Manufacturer: Pella Pharmaceuticals Co. Ltd
Category: otc | Type: HUMAN OTC DRUG LABEL
Date: 20241231

ACTIVE INGREDIENTS: ALPHA-ARBUTIN 10 mg/1 g
INACTIVE INGREDIENTS: JOJOBA OIL; SQUALENE; GLYCERIN; LAURETH-7; NIACINAMIDE; CITRIC ACID MONOHYDRATE; PHENOXYETHANOL; BENZOIC ACID; DEHYDROACETIC ACID; C13-14 ISOPARAFFIN; HYALURONATE SODIUM; GLYCYRRHIZA GLABRA; WATER; ETHYLHEXYLGLYCERIN

Intimate Brightening

Form and Presentation

Cream: Plastic Tube, 40 g

Active Ingredient

Alpha Arbutin

Inactive Ingredients

Aqua, Simmondsia Chinensis (Jojoba) Seed Oil, Squalene, Polyacrylamide, Phenoxyethanol, Glycerin, C13-14 Isoparaffin, Niacinamide (Vitamin B3), Glycyrrhiza Glabra (Licorice) Root Extract, Hyaluronic Acid, Laureth-7, Ethylhexylglycerin, Citric Acid, Parfum, Benzoic Acid, Dehydroacetic Acid.

Purpose

Whitening Cream for Sensitive Area

Properties

This product is formulated for use on all skin types and applicable to sensitive, intimate areas.

- Lightens, protects and rejuvenate the skin.
- Brings back the elasticity of the skin.
- Moisture the delicate skin.
- Soothes the skin in a pleasure way.
- Leaves a long-lasting refreshing aroma.

Paraben free

Indication

Intimate area brightening cream for women and men.

Precautions

Keep out of reach of children

Warnings

- For external use only.
- Over application will not increase results.
- If you have a sensitive skin test in a small area in the underarm before using on all your intimate areas.
- Discontinue if excessive redness or irritation occurs. If irritation persists, consult with a physician or pharmacist.
- Avoid direct contact with eyes, if contact occurs, rinse thoroughly with water.
- Do not apply to open wounds or mucous membranes.

Contraindications

Hypersensitivity to any of the components.

Side effects

It is well tolerated product there are no known side effects.

Dosage and Administration

Cleanse area with soap and water, and then gently exfoliate it with a loofah or sponge. This helps to remove any dead skin at the surface and allow the product to contact the fresh area that you want to whiten. Rinse the area and pat dry. Apply a small amount to fingertips and massage gently into the desired area that you are whitening. Allow time for it to absorb. After a few minutes, massage any excess cream into the area. Only use enough cream to apply a thin layer. Apply twice daily for maximum effectiveness.

Storage Conditions

Store below 30◦C.